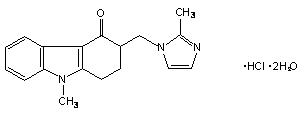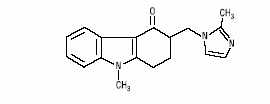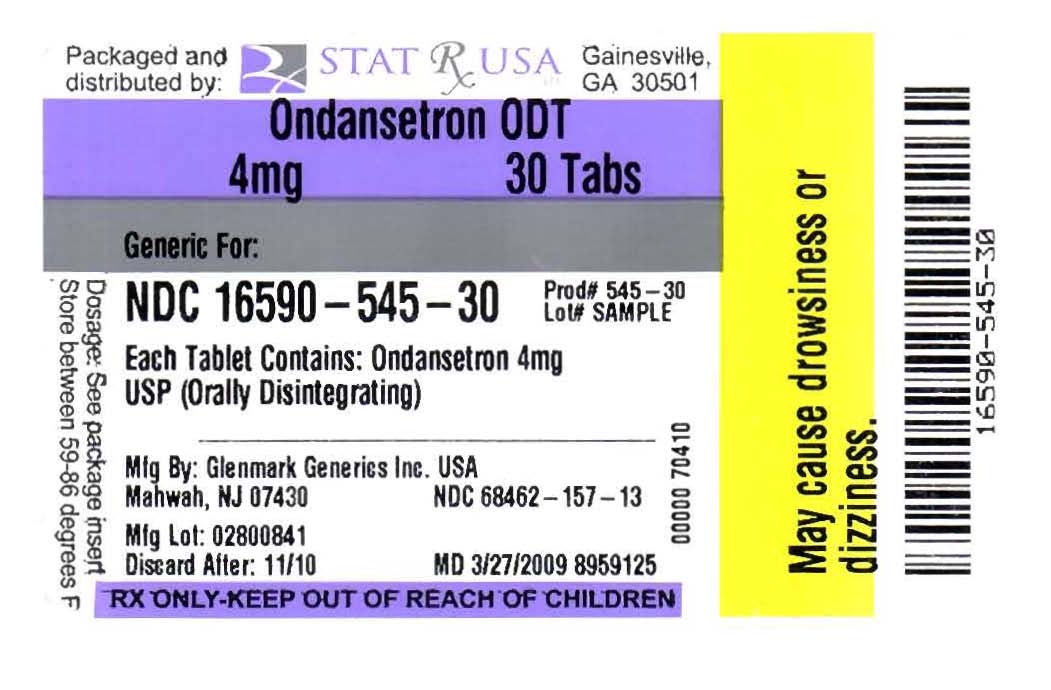 DRUG LABEL: Ondansetron
NDC: 16590-545 | Form: TABLET, ORALLY DISINTEGRATING
Manufacturer: Stat Rx USA
Category: prescription | Type: HUMAN PRESCRIPTION DRUG LABEL
Date: 20091027

ACTIVE INGREDIENTS: ONDANSETRON 4 mg/1 1

insert

DESCRIPTION

The active ingredient in ondansetron hydrochloride tablets is ondansetron hydrochloride (HCl) USP as the dihydrate, the racemic form of ondansetron and a selective blocking agent of the serotonin 5-HT3 receptor type. Chemically it is (±) 1, 2, 3, 9-tetrahydro-9-methyl-3-[(2-methyl-1H-imidazol-1-yl)methyl]-4H-carbazol-4-one, monohydrochloride, dihydrate. It has the following structural formula:

The empirical formula is C18H19N3O•HCl•2H2O, representing a molecular weight of 365.9.

Ondansetron HCl dihydrate USP is a white to off-white powder that is soluble in water and normal saline.

The active ingredient in ondansetron orally disintegrating tablets USP is ondansetron base, the racemic form of ondansetron, and a selective blocking agent of the serotonin 5-HT3 receptor type. Chemically it is (±) 1, 2, 3, 9-tetrahydro-9-methyl-3-[(2-methyl-1H-imidazol-1-yl)methyl]-4H-carbazol-4-one. It has the following structural formula:

The empirical formula is C18H19N3O representing a molecular weight of 293.4.

Each 4-mg ondansetron hydrochloride tablet for oral administration contains ondansetron HCl dihydrate USP equivalent to 4 mg of ondansetron. The dimensions for 4-mg ondansetron hydrochloride tablets are 10.10 x 5.60 mm. Each 8-mg ondansetron hydrochloride tablet for oral administration contains ondansetron HCl dihydrate USP equivalent to 8 mg of ondansetron. The dimensions for 8-mg ondansetron hydrochloride tablets are 10.10 x 5.60 mm. Each 24-mg ondansetron hydrochloride tablet for oral administration contains ondansetron HCl dihydrate USP equivalent to 24 mg of ondansetron. The dimensions for 24-mg ondansetron hydrochloride tablets are 14.10 x 7.60 mm. Each tablet also contains the inactive ingredients colloidal silicon dioxide, hypromellose, iron oxide yellow (8 mg tablet only), iron oxide red (24 mg tablet only), lactose monohydrate, magnesium stearate, microcrystalline cellulose, pregelatinized starch, titanium dioxide and triacetin.

Each 4-mg ondansetron orally disintegrating tablet USP for oral administration contains

4 mg ondansetron base. Each 8-mg ondansetron orally disintegrating tablet USP for oral administration contains 8 mg ondansetron base. Each ondansetron orally disintegrating tablet USP also contains the inactive ingredients aspartame, colloidal silicon dioxide, crospovidone, magnesium stearate, mannitol, sodium stearyl fumarate and strawberry flavor. Ondansetron orally disintegrating tablets USP are orally administered formulation of ondansetron which rapidly disintegrates on the tongue and does not require water to aid dissolution or swallowing. This product disintegrates in approximately 60 seconds.

CLINICAL PHARMACOLOGYPharmacodynamics:

Ondansetron is a selective 5-HT3 receptor antagonist. While its mechanism of action has not been fully characterized, ondansetron is not a dopamine-receptor antagonist. Serotonin receptors of the 5-HT3 type are present both peripherally on vagal nerve terminals and centrally in the chemoreceptor trigger zone of the area postrema. It is not certain whether ondansetron's antiemetic action is mediated centrally, peripherally, or in both sites. However, cytotoxic chemotherapy appears to be associated with release of serotonin from the enterochromaffin cells of the small intestine. In humans, urinary 5-HIAA (5-hydroxyindoleacetic acid) excretion increases after cisplatin administration in parallel with the onset of emesis. The released serotonin may stimulate the vagal afferents through the 5-HT3 receptors and initiate the vomiting reflex.

In animals, the emetic response to cisplatin can be prevented by pretreatment with an inhibitor of serotonin synthesis, bilateral abdominal vagotomy and greater splanchnic nerve section, or pretreatment with a serotonin 5-HT3 receptor antagonist.

In normal volunteers, single intravenous doses of 0.15 mg/kg of ondansetron had no effect on esophageal motility, gastric motility, lower esophageal sphincter pressure, or small intestinal transit time. Multiday administration of ondansetron has been shown to slow colonic transit in normal volunteers. Ondansetron has no effect on plasma prolactin concentrations.

Ondansetron does not alter the respiratory depressant effects produced by alfentanil or the degree of neuromuscular blockade produced by atracurium. Interactions with general or local anesthetics have not been studied.

Pharmacokinetics:

Ondansetron is well absorbed from the gastrointestinal tract and undergoes some first-pass metabolism. Mean bioavailability in healthy subjects, following administration of a single 8-mg tablet, is approximately 56%.

Ondansetron systemic exposure does not increase proportionately to dose. AUC from a 16-mg tablet was 24% greater than predicted from an 8-mg tablet dose. This may reflect some reduction of first-pass metabolism at higher oral doses. Bioavailability is also slightly enhanced by the presence of food but unaffected by antacids.

Ondansetron is extensively metabolized in humans, with approximately 5% of a radiolabeled dose recovered as the parent compound from the urine. The primary metabolic pathway is hydroxylation on the indole ring followed by subsequent glucuronide or sulfate conjugation. Although some nonconjugated metabolites have pharmacologic activity, these are not found in plasma at concentrations likely to significantly contribute to the biological activity of ondansetron.

In vitro metabolism studies have shown that ondansetron is a substrate for human hepatic cytochrome P-450 enzymes, including CYP1A2, CYP2D6, and CYP3A4. In terms of overall ondansetron turnover, CYP3A4 played the predominant role. Because of the multiplicity of metabolic enzymes capable of metabolizing ondansetron, it is likely that inhibition or loss of one enzyme (e.g., CYP2D6 genetic deficiency) will be compensated by others and may result in little change in overall rates of ondansetron elimination. Ondansetron elimination may be affected by cytochrome P-450 inducers. In a pharmacokinetic study of 16 epileptic patients maintained chronically on CYP3A4 inducers, carbamazepine, or phenytoin, reduction in AUC, Cmax, and T½ of ondansetron was observed.^1 This resulted in a significant increase in clearance. However, on the basis of available data, no dosage adjustment for ondansetron is recommended (see PRECAUTIONS: Drug interactions).

In humans, carmustine, etoposide, and cisplatin do not affect the pharmacokinetics of ondansetron.

Gender differences were shown in the disposition of ondansetron given as a single dose. The extent and rate of ondansetron's absorption is greater in women than men. Slower clearance in women, a smaller apparent volume of distribution (adjusted for weight), and higher absolute bioavailability resulted in higher plasma ondansetron levels. These higher plasma levels may in part be explained by differences in body weight between men and women. It is not known whether these gender-related differences were clinically important. More detailed pharmacokinetic information is contained in Tables 1 and 2 taken from 2 studies.

Table 1. Pharmacokinetics in Normal Volunteers: Single 8-mg Ondansetron Hydrochloride Tablet Dose
Age-group; (years) | Mean; Weight; (kg) | n | Peak Plasma; Concentration; (ng/mL) | Time of; Peak Plasma; Concentration; (h) | Mean; Elimination; Half-life; (h) | Systemic; Plasma; Clearance; L/h/kg | Absolute; Bioavailability
18-40 M; F | 69.0; 62.7 | 6; 5 | 26.2; 42.7 | 2.0; 1.7 | 3.1; 3.5 | 0.403; 0.354 | 0.483; 0.663
61-74 M; F | 77.5; 60.2 | 6; 6 | 24.1; 52.4 | 2.1; 1.9 | 4.1; 4.9 | 0.384; 0.255 | 0.585; 0.643
≥75 M; F | 78.0; 67.6 | 5; 6 | 37.0; 46.1 | 2.2; 2.1 | 4.5; 6.2 | 0.277; 0.249 | 0.619; 0.747

Table 2. Pharmacokinetics in Normal Volunteers: Single 24-mg Ondansetron Hydrochloride Tablet Dose
Age-group; (years) | Mean; Weight; (kg) | n | Peak Plasma; Concentration; (ng/mL) | Time of; Peak Plasma; Concentration; (h) | Mean; Elimination; Half-life; (h)
18-43 M; F | 84.1; 71.8 | 8; 8 | 125.8; 194.4 | 1.9; 1.6 | 4.7; 5.8

A reduction in clearance and increase in elimination half-life are seen in patients over 75 years of age. In clinical trials with cancer patients, safety and efficacy was similar in patients over 65 years of age and those under 65 years of age; there was an insufficient number of patients over 75 years of age to permit conclusions in that age-group. No dosage adjustment is recommended in the elderly.

In patients with mild-to-moderate hepatic impairment, clearance is reduced 2-fold and mean half-life is increased to 11.6 hours compared to 5.7 hours in normals. In patients with severe hepatic impairment (Child-Pugh^2 score of 10 or greater), clearance is reduced 2-fold to 3-fold and apparent volume of distribution is increased with a resultant increase in half-life to 20 hours. In patients with severe hepatic impairment, a total daily dose of 8 mg should not be exceeded.

Due to the very small contribution (5%) of renal clearance to the overall clearance, renal impairment was not expected to significantly influence the total clearance of ondansetron. However, ondansetron oral mean plasma clearance was reduced by about 50% in patients with severe renal impairment (creatinine clearance less 30 mL/min). This reduction in clearance is variable and was not consistent with an increase in half-life. No reduction in dose or dosing frequency in these patients is warranted.

Plasma protein binding of ondansetron as measured in vitro was 70% to 76% over the concentration range of 10 to 500 ng/mL. Circulating drug also distributes into erythrocytes.

Four-and 8-mg doses of ondansetron orally disintegrating tablets are bioequivalent to corresponding doses of ondansetron hydrochloride tablets and may be used interchangeably. One 24-mg ondansetron hydrochloride tablet is bioequivalent to and interchangeable with three 8-mg ondansetron hydrochloride tablets.

INDICATIONS AND USAGE

1. Prevention of nausea and vomiting associated with highly emetogenic cancer chemotherapy, including cisplatin ≥50 mg/m^2.
2. Prevention of nausea and vomiting associated with initial and repeat courses of moderately emetogenic cancer chemotherapy.
3. Prevention of nausea and vomiting associated with radiotherapy in patients receiving either total body irradiation, single high-dose fraction to the abdomen, or daily fractions to the abdomen.
4. Prevention of postoperative nausea and/or vomiting. As with other antiemetics, routine prophylaxis is not recommended for patients in whom there is little expectation that nausea and/or vomiting will occur postoperatively. In patients where nausea and/or vomiting must be avoided postoperatively, ondansetron hydrochloride tablets and ondansetron orally disintegrating tablets are recommended even where the incidence of postoperative nausea and/or vomiting is low.

CONTRAINDICATIONS

Ondansetron hydrochloride tablets and ondansetron orally disintegrating tablets are contraindicated for patients known to have hypersensitivity to the drug.

WARNINGS

Hypersensitivity reactions have been reported in patients who have exhibited hypersensitivity to other selective 5-HT3 receptor antagonists.

PRECAUTIONS

PRECAUTIONSGeneral

Ondansetron is not a drug that stimulates gastric or intestinal peristalsis. It should not be used instead of nasogastric suction. The use of ondansetron in patients following abdominal surgery or in patients with chemotherapy-induced nausea and vomiting may mask a progressive ileus and/or gastric distension.

Rarely and predominantly with intravenous ondansetron, transient ECG changes including QT interval prolongation have been reported.

Information for patients Phenylketonurics:

Phenylketonuric patients should be informed that ondansetron orally disintegrating tablets contain phenylalanine (a component of aspartame). Each 4 mg and 8 mg orally disintegrating tablet contains 1.5 mg and 3 mg of phenylalanine, respectively.

Patients should be instructed not to remove ondansetron orally disintegrating tablets from the blister until just prior to dosing. The tablet should not be pushed through the foil. With dry hands, the blister backing should be peeled completely off the blister. The tablet should be gently removed and immediately placed on the tongue to dissolve and be swallowed with the saliva. Peelable illustrated stickers are affixed to the product carton that can be provided with the prescription to ensure proper use and handling of the product.

Drug interactions

Ondansetron does not itself appear to induce or inhibit the cytochrome P-450 drug-metabolizing enzyme system of the liver (see CLINICAL PHARMACOLOGY: Pharmaceokinetica:). Because ondansetron is metabolized by hepatic cytochrome P-450 drug-metabolizing enzymes (CYP3A4, CYP2D6, CYP1A2), inducers or inhibitors of these enzymes may change the clearance and, hence, the half-life of ondansetron. On the basis of available data, no dosage adjustment is recommended for patients on these drugs.

Phenytoin, Carbamazepine, and Rifampicin: In patients treated with potent inducers of CYP3A4 (i.e., phenytoin, carbamazepine, and rifampicin), the clearance of ondansetron was significantly increased and ondansetron blood concentrations were decreased. However, on the basis of available data, no dosage adjustment for ondansetron is recommended for patients on these drugs.^1,3

Tramadol: Although no pharmacokinetic drug interaction between ondansetron and tramadol has been observed, data from 2 small studies indicate that ondansetron may be associated with an increase in patient controlled administration of tramadol.^4,5

Chemotherapy: Tumor response to chemotherapy in the P-388 mouse leukemia model is not affected by ondansetron. In humans, carmustine, etoposide, and cisplatin do not affect the pharmacokinetics of ondansetron.

In a crossover study in 76 pediatric patients, I.V. ondansetron did not increase blood levels of high-dose methotrexate.

Use in Surgical Patients: The coadministration of ondansetron had no effect on the pharmacokinetics and pharmacodynamics of temazepam.

Carcinogenesis, mutagenesis, impairment of fertility

Carcinogenic effects were not seen in 2-year studies in rats and mice with oral ondansetron doses up to 10 and 30 mg/kg/day, respectively. Ondansetron was not mutagenic in standard tests for mutagenicity. Oral administration of ondansetron up to 15 mg/kg/day did not affect fertility or general reproductive performance of male and female rats.

Pregnancy Teratogenic effects

Pregnancy Category B. Reproduction studies have been performed in pregnant rats and rabbits at daily oral doses up to 15 and 30 mg/kg/day, respectively, and have revealed no evidence of impaired fertility or harm to the fetus due to ondansetron. There are, however, no adequate and well-controlled studies in pregnant women. Because animal reproduction studies are not always predictive of human response, this drug should be used during pregnancy only if clearly needed.

Nursing mothers

Ondansetron is excreted in the breast milk of rats. It is not known whether ondansetron is excreted in human milk. Because many drugs are excreted in human milk, caution should be exercised when ondansetron is administered to a nursing woman.

Pediatric use

Little information is available about dosage in pediatric patients 4 years of age or younger (see CLINICAL PHARMACOLGY and DOSAGE AND ADMINISTRATIONsections for use in pediatric patients 4 to 18 years of age).

Geriatric use

Of the total number of subjects enrolled in cancer chemotherapy-induced and postoperative nausea and vomiting in US- and foreign-controlled clinical trials, for which there were subgroup analyses, 938 were 65 years of age and over. No overall differences in safety or effectiveness were observed between these subjects and younger subjects, and other reported clinical experience has not identified differences in responses between the elderly and younger patients, but greater sensitivity of some older individuals cannot be ruled out. Dosage adjustment is not needed in patients over the age of 65 (see CLINICAL PHARMACOLGY.

ADVERSE REACTIONS

The following have been reported as adverse events in clinical trials of patients treated with ondansetron, the active ingredient of ondansetron hydrochloride. A causal relationship to therapy with ondansetron hydrochloride has been unclear in many cases.

Chemotherapy-Induced Nausea and Vomiting:

The adverse events in Table 5 have been reported in 5% of adult patients receiving a single 24-mg ondansetron hydrochloride tablet in 2 trials. These patients were receiving concurrent highly emetogenic cisplatin-based chemotherapy regimens (cisplatin dose 50 mg/m^2).

Table 5. Principal Adverse Events in US Trials: Single Day Therapy With 24-mg Ondansetron Hydrochloride Tablets (Highly Emetogenic Chemotherapy)
Event | Ondansetron; 24 mg q.d.; n = 300 | Ondansetron; 8 mg b.i.d.; n = 124 | Ondansetron; 32 mg q.d.; n = 117
Headache | 33 (11%) | 16 (13%) | 17 (15%)
Diarrhea | 13 (4%) | 9 (7%) | 3 (3%)

The adverse events in Table 6 have been reported in 5% of adults receiving either 8 mg of ondansetron hydrochloride tablets 2 or 3 times a day for 3 days or placebo in 4 trials. These patients were receiving concurrent moderately emetogenic chemotherapy, primarily cyclophosphamide-based regimens.

Table 6. Principal Adverse Events in US Trials: 3 Days of Therapy With 8-mg Ondansetron Hydrochloride Tablets (Moderately Emetogenic Chemotherapy)
Event | Ondansetron 8 mg b.i.d.; n = 242 | Ondansetron 8 mg t.i.d.; n = 415 | Placebo; n = 262
Headache | 58 (24%) | 113 (27%) | 34 (13%)
Malaise/fatigue | 32 (13%) | 37 (9%) | 6 (2%)
Constipation | 22 (9%) | 26 (6%) | 1 (1%)
Diarrhea | 15 (6%) | 16 (4%) | 10 (4%)
Dizziness | 13 (5%) | 18 (4%) | 12 (5%)

Central Nervous System:

There have been rare reports consistent with, but not diagnostic of, extrapyramidal reactions in patients receiving ondansetron.

Hepatic:

In 723 patients receiving cyclophosphamide-based chemotherapy in US clinical trials, AST and/or ALT values have been reported to exceed twice the upper limit of normal in approximately 1% to 2% of patients receiving ondansetron hydrochloride tablets. The increases were transient and did not appear to be related to dose or duration of therapy. On repeat exposure, similar transient elevations in transaminase values occurred in some courses, but symptomatic hepatic disease did not occur. The role of cancer chemotherapy in these biochemical changes cannot be clearly determined.

There have been reports of liver failure and death in patients with cancer receiving concurrent medications including potentially hepatotoxic cytotoxic chemotherapy and antibiotics. The etiology of the liver failure is unclear.

Integumentary:

Rash has occurred in approximately 1% of patients receiving ondansetron.

Other:

Rare cases of anaphylaxis, bronchospasm, tachycardia, angina (chest pain), hypokalemia, electrocardiographic alterations, vascular occlusive events, and grand mal seizures have been reported. Except for bronchospasm and anaphylaxis, the relationship to ondansetron hydrochloride was unclear.

Radiation-Induced Nausea and Vomiting:

The adverse events reported in patients receiving ondansetron hydrochloride tablets and concurrent radiotherapy were similar to those reported in patients receiving ondansetron hydrochloride tablets and concurrent chemotherapy. The most frequently reported adverse events were headache, constipation, and diarrhea.

Postoperative Nausea and Vomiting:

The adverse events in Table 7 have been reported in 5% of patients receiving ondansetron hydrochloride tablets at a dosage of 16 mg orally in clinical trials. With the exception of headache, rates of these events were not significantly different in the ondansetron and placebo groups. These patients were receiving multiple concomitant perioperative and postoperative medications.

Table 7. Frequency of Adverse Events From Controlled Studies With Ondansetron Hydrochloride Tablets (Postoperative Nausea and Vomiting)
Adverse Event | Ondansetron 16 mg; (n = 550) | Placebo; (n = 531)
Wound problem | 152 (28%) | 162 (31%)
Drowsiness/sedation | 112 (20%) | 122 (23%)
Headache | 49 (9%) | 27 (5%)
Hypoxia | 49 (9%) | 35 (7%)
Pyrexia | 45 (8%) | 34 (6%)
Dizziness | 36 (7%) | 34 (6%)
Gynecological disorder | 36 (7%) | 33 (6%)
Anxiety/agitation | 33 (6%) | 29 (5%)
Bradycardia | 32 (6%) | 30 (6%)
Shiver(s) | 28 (5%) | 30 (6%)
Urinary retention | 28 (5%) | 18 (3%)
Hypotension | 27 (5%) | 32 (6%)
Pruritus | 27 (5%) | 20 (4%)

Preliminary observations in a small number of subjects suggest a higher incidence of headache when ondansetron orally disintegrating tablets are taken with water, when compared to without water.

Observed During Clinical Practice:

In addition to adverse events reported from clinical trials, the following events have been identified during post-approval use of oral formulations of ondansetron hydrochloride. Because they are reported voluntarily from a population of unknown size, estimates of frequency cannot be made. The events have been chosen for inclusion due to a combination of their seriousness, frequency of reporting, or potential causal connection to ondansetron hydrochloride.

Cardiovascular: Rarely and predominantly with intravenous ondansetron, transient ECG changes including QT interval prolongation have been reported.

General: Flushing. Rare cases of hypersensitivity reactions, sometimes severe (e.g., anaphylaxis/anaphylactoid reactions, angioedema, bronchospasm, shortness of breath, hypotension, laryngeal edema, stridor) have also been reported. Laryngospasm, shock, and cardiopulmonary arrest have occurred during allergic reactions in patients receiving injectable ondansetron.

Hepatobiliary: Liver enzyme abnormalities

Lower Respiratory: Hiccups

Neurology: Oculogyric crisis, appearing alone, as well as with other dystonic reactions

Skin: Urticaria

Special Senses: Eye Disorders:Cases of transient blindness, predominantly during intravenous administration, have been reported. These cases of transient blindness were reported to resolve within a few minutes up to 48 hours

OVERDOSAGE

There is no specific antidote for ondansetron overdose. Patients should be managed with appropriate supportive therapy. Individual intravenous doses as large as 150 mg and total daily intravenous doses as large as 252 mg have been inadvertently administered without significant adverse events. These doses are more than 10 times the recommended daily dose.

In addition to the adverse events listed above, the following events have been described in the setting of ondansetron overdose: “Sudden blindness” (amaurosis) of 2 to 3 minutes’ duration plus severe constipation occurred in 1 patient that was administered 72 mg of ondansetron intravenously as a single dose. Hypotension (and faintness) occurred in a patient that took 48 mg of ondansetron hydrochloride tablets. Following infusion of 32 mg over only a 4-minute period, a vasovagal episode with transient second-degree heart block was observed. In all instances, the events resolved completely.

DOSAGE AND ADMINISTRATION

DOSAGE AND ADMINISTRATIONInstructions for Use/Handling ondansetron orally disintegrating tablets:

Do not attempt to push ondansetron orally disintegrating tablets through the foil backing. With dry hands, PEEL BACK the foil backing of 1 blister and GENTLY remove the tablet. IMMEDIATELY place the ondansetron orally disintegrating tablet on top of the tongue where it will dissolve in seconds, then swallow with saliva. Administration with liquid is not necessary.

Prevention of Nausea and Vomiting Associated With Highly Emetogenic Cancer Chemotherapy:

The recommended adult oral dosage of ondansetron hydrochloride is 24 mg given as three 8-mg tablets administered 30 minutes before the start of single-day highly emetogenic chemotherapy, including cisplatin ≥50 mg/m^2. Multiday, single-dose administration of a 24 mg dosage has not been studied.

Pediatric Use:

There is no experience with the use of a 24 mg dosage in pediatric patients.

Geriatric Use:

The dosage recommendation is the same as for the general population.

Prevention of Nausea and Vomiting Associated With Moderately Emetogenic Cancer Chemotherapy:

The recommended adult oral dosage is one 8-mg ondansetron hydrochloride tablet or one 8-mg ondansetron orally disintegrating tablet given twice a day. The first dose should be administered 30 minutes before the start of emetogenic chemotherapy, with a subsequent dose 8 hours after the first dose. One 8-mg ondansetron hydrochloride tablet or one 8-mg ondansetron orally disintegrating tablet should be administered twice a day (every 12 hours) for 1 to 2 days after completion of chemotherapy.

Pediatric Use:

For pediatric patients 12 years of age and older, the dosage is the same as for adults. For pediatric patients 4 through 11 years of age, the dosage is one 4-mg ondansetron hydrochloride tablet or one 4-mg ondansetron orally disintegrating tablet given 3 times a day. The first dose should be administered 30 minutes before the start of emetogenic chemotherapy, with subsequent doses 4 and 8 hours after the first dose. One 4-mg ondansetron hydrochloride tablet or one 4-mg ondansetron orally disintegrating tablet should be administered 3 times a day (every 8 hours) for 1 to 2 days after completion of chemotherapy.

Geriatric Use:

The dosage is the same as for the general population.

Prevention of Nausea and Vomiting Associated With Radiotherapy, Either Total Body Irradiation, or Single High-Dose Fraction or Daily Fractions to the Abdomen:

The recommended oral dosage is one 8-mg ondansetron hydrochloride tablet or one 8-mg ondansetron orally disintegrating tablet given 3 times a day.

For total body irradiation, one 8-mg ondansetron hydrochloride tablet or one 8-mg ondansetron orally disintegrating tablet should be administered 1 to 2 hours before each fraction of radiotherapy administered each day.

For single high-dose fraction radiotherapy to the abdomen, one 8-mg ondansetron hydrochloride tablet or one 8-mg ondansetron orally disintegrating tablet should be administered 1 to 2 hours before radiotherapy, with subsequent doses every 8 hours after the first dose for 1 to 2 days after completion of radiotherapy.

For daily fractionated radiotherapy to the abdomen, one 8-mg ondansetron hydrochloride tablet or one 8-mg ondansetron orally disintegrating tablet should be administered 1 to 2 hours before radiotherapy, with subsequent doses every 8 hours after the first dose for each day radiotherapy is given.

Pediatric Use:

There is no experience with the use of ondansetron hydrochloride tablets or ondansetron orally disintegrating tablets in the prevention of radiation-induced nausea and vomiting in pediatric patients.

Geriatric Use:

The dosage recommendation is the same as for the general population.

Postoperative Nausea and Vomiting:

The recommended dosage is 16 mg given as two 8-mg ondansetron hydrochloride tablets or two 8-mg ondansetron orally disintegrating tablets 1 hour before induction of anesthesia.

Pediatric Use:

There is no experience with the use of ondansetron hydrochloride tablets or ondansetron orally disintegrating tablets in the prevention of postoperative nausea and vomiting in pediatric patients.

Geriatric Use:

The dosage is the same as for the general population.

Dosage Adjustment for Patients With Impaired Renal Function:

The dosage recommendation is the same as for the general population. There is no experience beyond first-day administration of ondansetron.

Dosage Adjustment for Patients With Impaired Hepatic Function:

In patients with severe hepatic impairment (Child-Pugh^2 score of 10 or greater), clearance is reduced and apparent volume of distribution is increased with a resultant increase in plasma half-life. In such patients, a total daily dose of 8 mg should not be exceeded.

HOW SUPPLIED

Ondansetron hydrochloride tablets, 4 mg (ondansetron HCl dihydrate USP equivalent to 4 mg of ondansetron), are white, oval, standard convex, film-coated tablets with ‘4’ on one side and ‘G1’ logo on the other side in :

Bottles of 30 tablets (NDC 68462-105-30).
Carton containing 1 card with 3 unit of use blisters (NDC 68462-105-33).

Ondansetron hydrochloride tablets, 8 mg (ondansetron HCl dihydrate USP equivalent to 8 mg of ondansetron), are yellow, oval, standard convex, film-coated tablets with ‘8’ on one side and ‘G1’ logo on the other side in :

Bottles of 30 tablets (NDC 68462-106-30).
Carton containing 1 card with 3 unit of use blisters (NDC 68462-106-33).

Bottles: Store at 20º - 25ºC (68º - 77ºF) (See USP Controlled Room Temperature). Dispense in a tight, light-resistant container as defined in the USP.

Carton: Store at 20º - 25ºC (68º - 77ºF) (See USP Controlled Room Temperature). Protect from light. Store blister in carton.

Ondansetron hydrochloride tablets, 24 mg (ondansetron HCl dihydrate USP equivalent to 24 mg of ondansetron), are pink, oval, standard convex, film-coated tablets with ‘24’ on one side and ‘G1’ logo on the other side in daily unit dose packs of 1 tablet (NDC 68462-107-40).

Store at 20º - 25ºC (68º - 77ºF) (See USP Controlled Room Temperature).

Ondansetron orally disintegrating tablets USP, 4 mg (as 4 mg ondansetron base) are white, circular, flat faced, uncoated tablets with ‘G’ engraved on one side and ‘4’ on the other side in unit dose packs of 30 tablets (NDC 68462-157-13).

Ondansetron orally disintegrating tablets USP, 8 mg (as 8 mg ondansetron base) are white, circular, flat faced, uncoated tablets with ‘G’ engraved on one side and ‘8’ on the other side in unit dose packs of 10 tablets (NDC 68462-158-11) and 30 tablets (NDC 68462-158-13).

Store at 20°-25°C (68°- 77°F) (See USP Controlled Room Temperature).

REFERENCES

1. Britto MR, Hussey EK, Mydlow P, et al. Effect of enzyme inducers on ondansetron (OND) metabolism in humans. Clin Pharmacol Ther. 1997;61:228.
2. Pugh RNH, Murray-Lyon IM, Dawson JL, Pietroni MC, Williams R. Transection of the oesophagus for bleeding oesophageal varices. Brit J Surg. 1973;60:646-649.
3. Villikka K, Kivisto KT, Neuvonen PJ. The effect of rifampin on the pharmacokinetics of oral and intravenous ondansetron. Clin Pharmacol Ther. 1999;65:377-381.
4. De Witte JL, Schoenmaekers B, Sessler DI, et al. Anesth Analg. 2001;92:1319-1321.
5. Arcioni R, della Rocca M, Romanò R, et al. Anesth Analg. 2002;94:1553-1557.

Manufactured by:

Glenmark Generics Ltd.
Colvale-Bardez, Goa 403 513, India

Information for patients Phenylketonurics:

Phenylketonuric patients should be informed that ondansetron orally disintegrating tablets contain phenylalanine (a component of aspartame). Each 4 mg and 8 mg orally disintegrating tablet contains 1.5 mg and 3 mg of phenylalanine, respectively.

Patients should be instructed not to remove ondansetron orally disintegrating tablets from the blister until just prior to dosing. The tablet should not be pushed through the foil. With dry hands, the blister backing should be peeled completely off the blister. The tablet should be gently removed and immediately placed on the tongue to dissolve and be swallowed with the saliva. Peelable illustrated stickers are affixed to the product carton that can be provided with the prescription to ensure proper use and handling of the product.

Drug interactions

Ondansetron does not itself appear to induce or inhibit the cytochrome P-450 drug-metabolizing enzyme system of the liver (seeCLINICAL PHARMACOLOGY: Pharmacokinetics:). Because ondansetron is metabolized by hepatic cytochrome P-450 drug-metabolizing enzymes (CYP3A4, CYP2D6, CYP1A2), inducers or inhibitors of these enzymes may change the clearance and, hence, the half-life of ondansetron. On the basis of available data, no dosage adjustment is recommended for patients on these drugs.

Phenytoin, Carbamazepine, and Rifampicin: In patients treated with potent inducers of CYP3A4 (i.e., phenytoin, carbamazepine, and rifampicin), the clearance of ondansetron was significantly increased and ondansetron blood concentrations were decreased. However, on the basis of available data, no dosage adjustment for ondansetron is recommended for patients on these drugs.^1,3

Tramadol: Although no pharmacokinetic drug interaction between ondansetron and tramadol has been observed, data from 2 small studies indicate that ondansetron may be associated with an increase in patient controlled administration of tramadol.^4,5

Chemotherapy: Tumor response to chemotherapy in the P-388 mouse leukemia model is not affected by ondansetron. In humans, carmustine, etoposide, and cisplatin do not affect the pharmacokinetics of ondansetron.

In a crossover study in 76 pediatric patients, I.V. ondansetron did not increase blood levels of high-dose methotrexate.

Use in Surgical Patients: The coadministration of ondansetron had no effect on the pharmacokinetics and pharmacodynamics of temazepam.

Carcinogenesis, mutagenesis, impairment of fertility

Carcinogenic effects were not seen in 2-year studies in rats and mice with oral ondansetron doses up to 10 and 30 mg/kg/day, respectively. Ondansetron was not mutagenic in standard tests for mutagenicity. Oral administration of ondansetron up to 15 mg/kg/day did not affect fertility or general reproductive performance of male and female rats.

Pregnancy Teratogenic effects

Pregnancy Category B. Reproduction studies have been performed in pregnant rats and rabbits at daily oral doses up to 15 and 30 mg/kg/day, respectively, and have revealed no evidence of impaired fertility or harm to the fetus due to ondansetron. There are, however, no adequate and well-controlled studies in pregnant women. Because animal reproduction studies are not always predictive of human response, this drug should be used during pregnancy only if clearly needed.

Nursing mothers

Ondansetron is excreted in the breast milk of rats. It is not known whether ondansetron is excreted in human milk. Because many drugs are excreted in human milk, caution should be exercised when ondansetron is administered to a nursing woman.

Pediatric use

Little information is available about dosage in pediatric patients 4 years of age or younger (see CLINICAL PHARMACOLOGY and DOSAGE AND ADMINISTRATION sections for use in pediatric patients 4 to 18 years of age).

Geriatric use

Of the total number of subjects enrolled in cancer chemotherapy-induced and postoperative nausea and vomiting in US- and foreign-controlled clinical trials, for which there were subgroup analyses, 938 were 65 years of age and over. No overall differences in safety or effectiveness were observed between these subjects and younger subjects, and other reported clinical experience has not identified differences in responses between the elderly and younger patients, but greater sensitivity of some older individuals cannot be ruled out. Dosage adjustment is not needed in patients over the age of 65 (see CLINICAL PHARMACOLOGY.

LABEL IMAGE